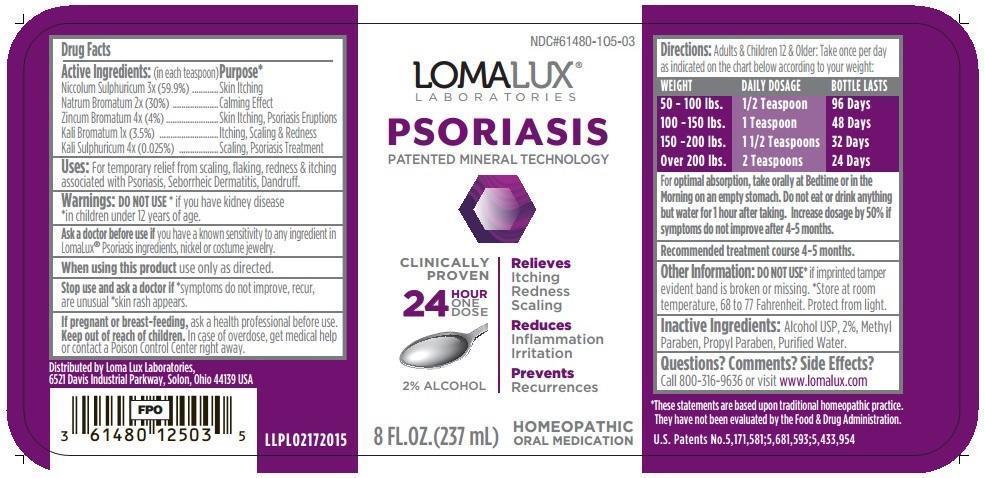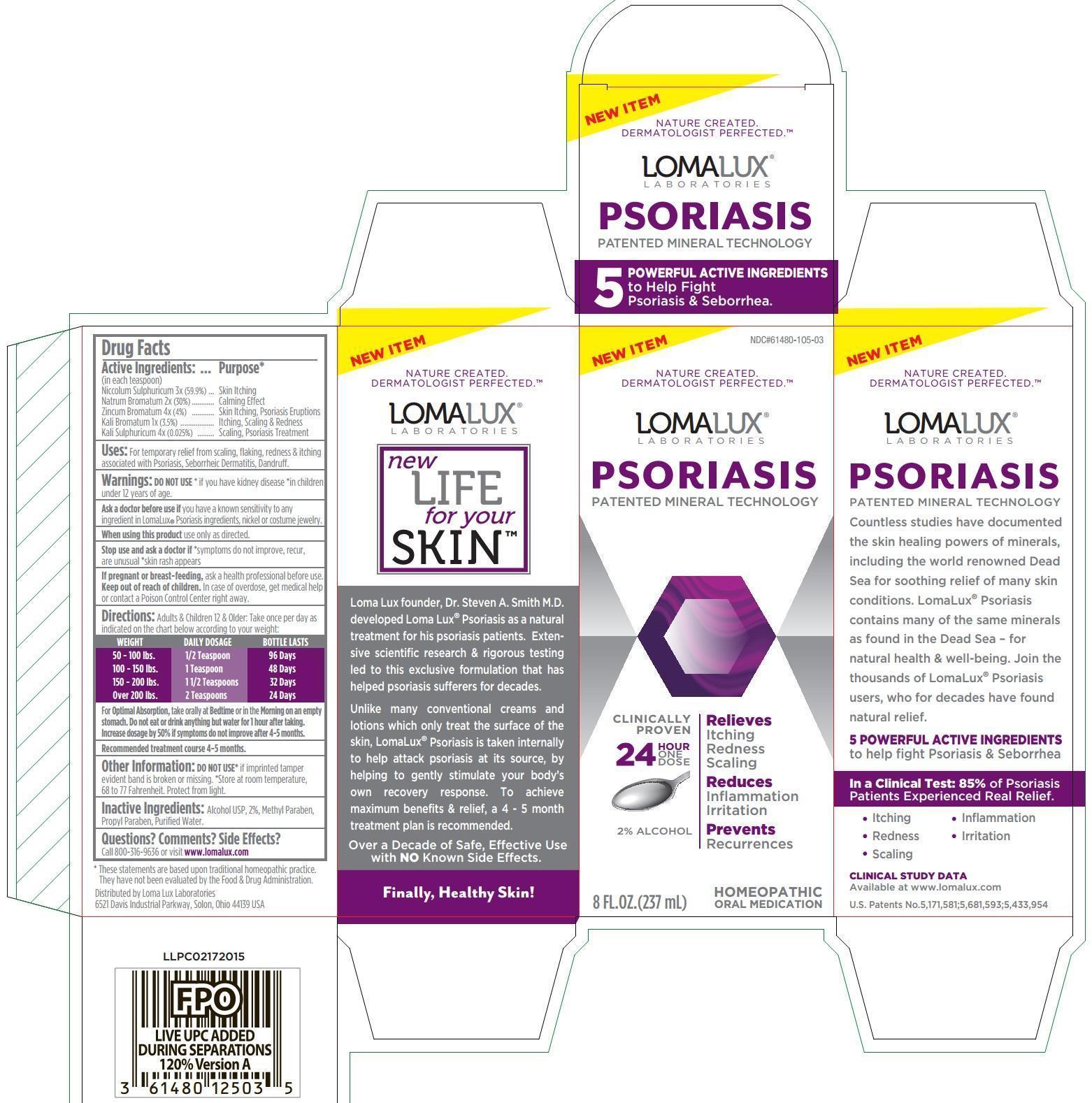 DRUG LABEL: PSORIASIS
NDC: 61480-105 | Form: LIQUID
Manufacturer: PLYMOUTH HEALTHCARE PRODUCTS LLC
Category: homeopathic | Type: HUMAN OTC DRUG LABEL
Date: 20251120

ACTIVE INGREDIENTS: NICKEL SULFATE HEXAHYDRATE 3 [hp_X]/237 mL; SODIUM BROMIDE 2 [hp_X]/237 mL; ZINC BROMIDE 4 [hp_X]/237 mL; POTASSIUM BROMIDE 1 [hp_X]/237 mL; POTASSIUM SULFATE 4 [hp_X]/237 mL
INACTIVE INGREDIENTS: METHYLPARABEN; PROPYLPARABEN; WATER; ALCOHOL

LOMA LUX PSORIASIS

Drug Facts

Active Ingredients (in each teaspoon): | Purpose*
Niccolum Sulphuricum 3x (59.9%) | Skin Itching
Natrum Bromatum 2x (30%) | Calming Effect
Zincum Bromatum 4x (4%) | Skin Itching, Psoriasis Eruptions
Kali Bromatum 1x (3.5%) | Itching, Scaling & Redness
Kali Sulphuricum 4x (0.025%) | Scaling, Psoriasis Treatment

INDICATIONS AND USAGE

Uses: For temporary relief from scaling, flaking, redness & itching associated with Psoriasis, Seborrheic Dermatitis, Dandruff.

Warnings:

- DO NOT USE* if you have kidney disease *in children under 12 years of age.
- Ask a doctor before use ifyou have a known sensitivity to any ingredient in LomaLux® Psoriasis ingredients, nickel or costume jewelry.
- When using this productuse only as directed.
- Stop use and ask a doctor if*symptoms do not improve, recur, are unusual *skin rash appears
- If pregnant or breast-feeding,ask a health professional before use.

- Keep out of reach of children.In case of overdose, get medical help or contact a Poison Control Center right away.

DOSAGE AND ADMINISTRATION

Directions:Adults & Children 12 & Older: Take once per day as indicated on the chart below according to your weight:

WEIGHT DAILY DOSAGE BOTTLE LASTS

50 - 100 lbs. 1/2 Teaspoon 96 Days

100 - 150 lbs. 1 Teaspoon 48 Days

150 - 200 lbs. 1 1/2 Teaspoons 32 Days

Over 200 lbs. 2 Teaspoons 24 Days

For Optimal Absorption, take orally at Bedtime or in the Morning on an empty stomach. Do not eat or drink anything but water for 1 hour after taking. Increase dosage by 50% if symptoms do not improve after 4-5 months.

Recommended treatment course 4-5 months.

Other Information: DO NOT USE*if imprinted tamper evident band is broken or missing. *Store at room temperature, 68 to 77 Fahrenheit. Protect from light.

INACTIVE INGREDIENT

Inactive Ingredients:Alcohol USP 2%, Methyl Paraben, Propyl Paraben, Purified Water.

Questions? Comments? Side Effects?

Call 800-316-9636 or visit www.lomalux.com

OTHER SAFETY INFORMATION

*These statements are based upon traditional homeopathic practice. They have not been evaluated by the Food & Drug Administration.

Distributed by Loma Lux Laboratories

6521 Davis Industrial Parkway, Solon, Ohio 44139 USA

Loma Lux founder, Dr. Steven A. Smith M.D. developed Loma Lux® Psoriasis as a natural treatment for his psoriasis patients. Extensive scientific research & rigorous testing led to this exclusive formulation that has helped psoriasis sufferers for decates.

Unlike many conventional creams and lotions which only treat the surface of the skin, LomaLux Psoriasis is taken internally to help attack psoriasis at its source, by helping to gently stimulate your body's own recovery response. To achieve maximum benefits & relief, a 4-5 month treatment plan is recommended.

Over a Decade of Safe, Effective Use with NO Known Side Effects.

Finally, Healthy Skin!

Countless Studies have documented the skin healing powers of minerals, including the world renowned Dead Sea for soothing relief of many skin conditions. LomaLux® Psoriasis contains many of the same minerals as found in the Dead Sea - for natural health & well-being. Join the thousands of LomaLux® Psoriasis users, who for decades have found natural relief.

5 POWERFUL ACTIVE INGREDIENTS to help fight Psoriasis & Seborrhea

In a Clinical Test: 85% of Psoriasis Patients Experienced Real Relief.

- Itching
- Redness
- Scaling
- Inflammation
- Irritation

CLINICAL STUDY DATA available at www.lomalux.com

U.S. Patents No.5,171,581;5,681,593;5,433,954

PACKAGE LABEL

NEW ITEM

NDC#61480-105-03

NATURE CREATED. DERMATOLOGIST PERFECTED.™

LOMALUX® LABORATORIES

PSORIASIS

PATENTED MINERAL TECHNOLOGY

CLINICALLY PROVEN

Relieves

Itching

Redness

Scaling

Reduces

Inflammation

Irritation

Prevents

Recurrences

24 HOUR ONE DOSE

2% Alcohol

8 FL. OZ. (237 mL)

HOMEOPATHIC ORAL MEDICATION

PURPOSE

Relieves

Itching

Redness

Scaling

Reduces

Inflammation

Irritation

Prevents

Recurrences